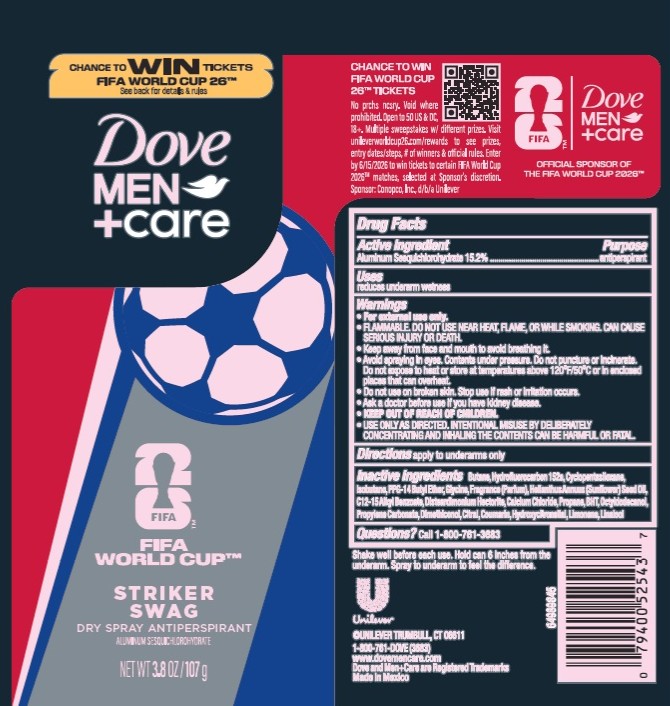 DRUG LABEL: Dove Men Care
NDC: 64942-2409 | Form: AEROSOL, SPRAY
Manufacturer: Conopco d/b/a Unilever
Category: otc | Type: HUMAN OTC DRUG LABEL
Date: 20251203

ACTIVE INGREDIENTS: ALUMINUM SESQUICHLOROHYDRATE 15.2 g/100 g
INACTIVE INGREDIENTS: C12-15 ALKYL BENZOATE; CALCIUM CHLORIDE; PPG-14 BUTYL ETHER; DISTEARDIMONIUM HECTORITE; ISOBUTANE; LIMONENE, (+)-; HELIANTHUS ANNUUS (SUNFLOWER) SEED OIL; PROPYLENE CARBONATE; LINALOOL; COUMARIN; HYDROXYCITRONELLAL; BUTANE; GLYCINE; HYDROFLUOROCARBON 152A; CYCLOPENTASILOXANE; DIMETHICONOL (40 CST); OCTYLDODECANOL; CITRAL; PROPANE; BHT

Dove Men + Care Fifa World Cup Striker Swag Dry Spray Antiperspirant

DESCRIPTION

Dove Men + Care Fifa World Cup Striker Swag Dry Spray Antiperspirant

ACTIVE INGREDIENT

Aluminum Sesquichlorohydrate 15.2%

PURPOSE

Antiperspirant

INDICATIONS AND USAGE

reduces underarm wetness

WARNINGS

• For external use only.
• FLAMMABLE. DO NOT USE NEAR HEAT, FLAME, OR WHILE SMOKING. CAN CAUSE SERIOUS INJURY OR DEATH.
• Keep away from face and mouth to avoid breathing it.
• Avoid spraying in eyes. Contents under pressure. Do not puncture or incinerate. Do not expose to heat or store at temperatures above 120°F/50°C or in enclosed places that can overheat.
• Do not use on broken skin. • Stop use if rash or irritation occurs.• Ask a doctor before use if you have kidney disease. • USE ONLY AS DIRECTED. INTENTIONAL MISUSE BY DELIBERATELY CONCENTRATING AND INHALING THE CONTENTS CAN BE HARMFUL OR FATAL.

• KEEP OUT OF REACH OF CHILDREN.

DOSAGE AND ADMINISTRATION

apply to underarms only

INACTIVE INGREDIENT

Butane,Hydrofluorocarbon 152a,Cyclopentasiloxane,
Isobutane,PPG-14 Butyl Ether,Glycine,Fragrance (Parfum),Helianthus Annuus (Sunflower) Seed Oil,
C12-15 Alkyl Benzoate,Disteardimonium Hectorite,Calcium Chloride,Propane,BHT,Octyldodecanol,
Propylene Carbonate,Dimethiconol,Citral,Coumarin,Hydroxycitronellal,Limonene,Linalool

QUESTIONS

Call 1-800-761-3683